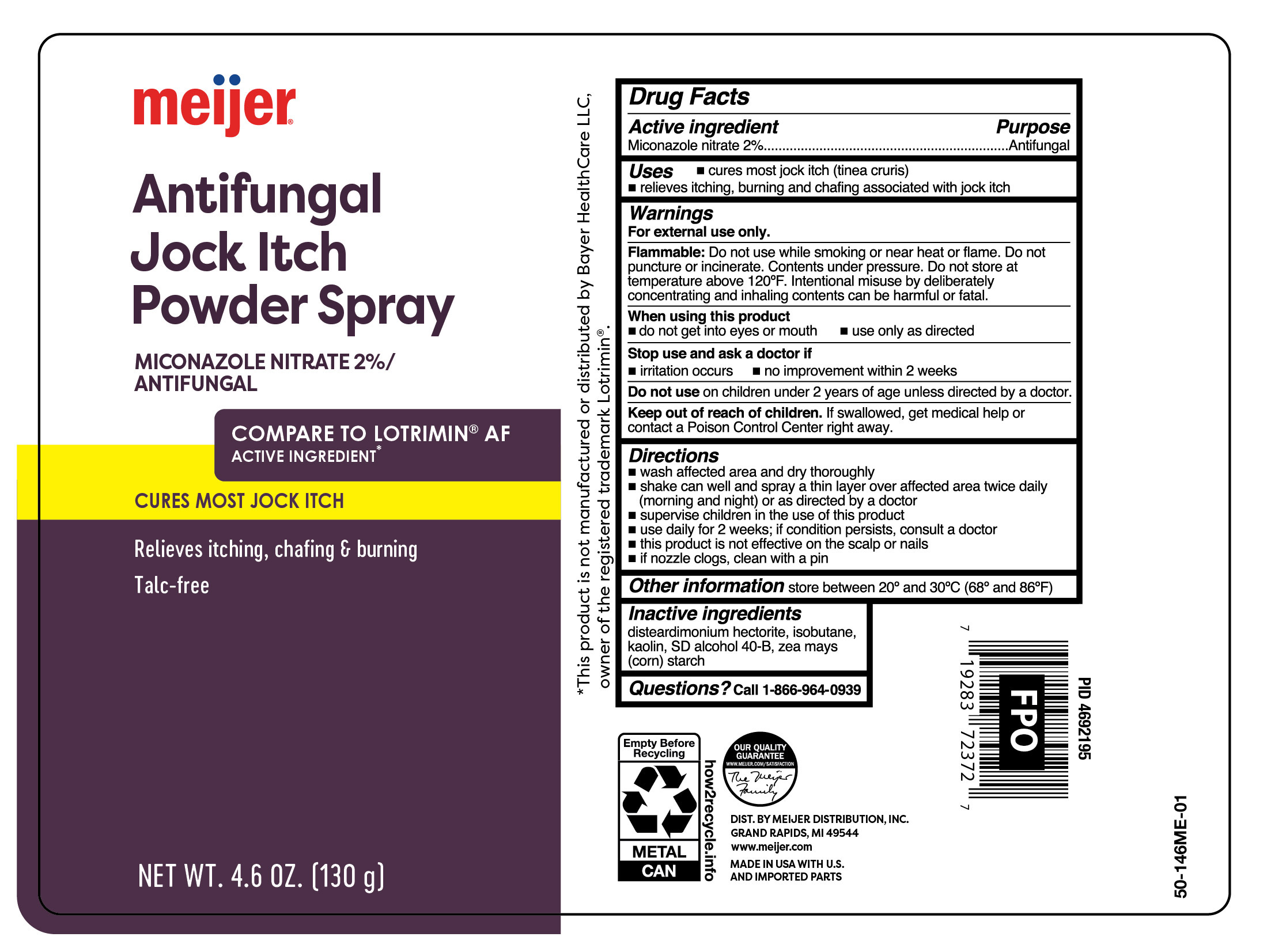 DRUG LABEL: Jock Itch
NDC: 79481-0602 | Form: AEROSOL, SPRAY
Manufacturer: Meijer Distribution Inc.
Category: otc | Type: HUMAN OTC DRUG LABEL
Date: 20251030

ACTIVE INGREDIENTS: MICONAZOLE NITRATE 20 mg/1 g
INACTIVE INGREDIENTS: DISTEARDIMONIUM HECTORITE; KAOLIN; ALCOHOL; ISOBUTANE; ZEA MAYS SUBSP. MAYS WHOLE

Meijer Jock Itch Miconazole Nitrate Antifungal Powder Spray - Talc Free

Active ingredients

Miconazole nitrate 2%

Purpose

Antifungal

Uses

- cures most jock itch (tinea cruris)
- relieves itching, burning and chafing associated with jock itch

Warnings

For external use only.

Flammable:

Do not use while smoking or near heat or flame. Do not puncture or incinerate. Contents under pressure. Do not store at temperature above 120°F. Intentional misuse by deliberately concentrating and inhaling contents can be harmful or fatal.

When using this product

- do not get into eyes or mouth
- use only as directed

Stop use and ask a doctor if

- irritation occurs
- no improvement within 2 weeks

Do not use

on children under 2 years of age unless directed by a doctor.

Keep out of reach of children.

If swallowed, get medical help or contact a Poison Control Center right away.

Directions

- wash affected area and dry thoroughly
- shake can well and spray a thin layer over affected area twice daily (morning and night) or as directed by a doctor
- supervise children in the use of this product
- use daily for 2 weeks; if condition persists, consult a doctor
- this product is not effective on the scalp or nails
- if nozzle clogs, clean with a pin

Other information

store between 20° and 30°C (68° and 86°F)

Inactive ingredients

disteardimonium hectorite, isobutane, kaolin, SD alcohol 40-B, zea mays (corn) starch

Questions?

Call 1-866-964-0939

Principal Display Panel

meijer

ANTIFUNGAL

jock itch

Powder Spray

Miconazole Nitrate 2% | Antifungal

TALC-FREE

Cures most jock itch

Relieves itching, chafing & burning

NET WT. 4.6 OZ (130 g)